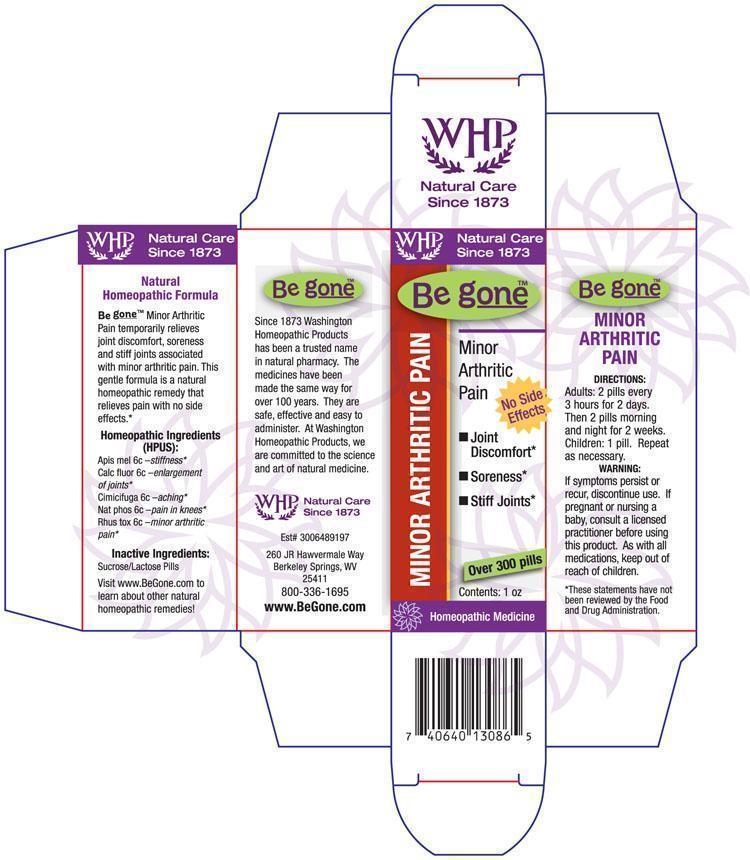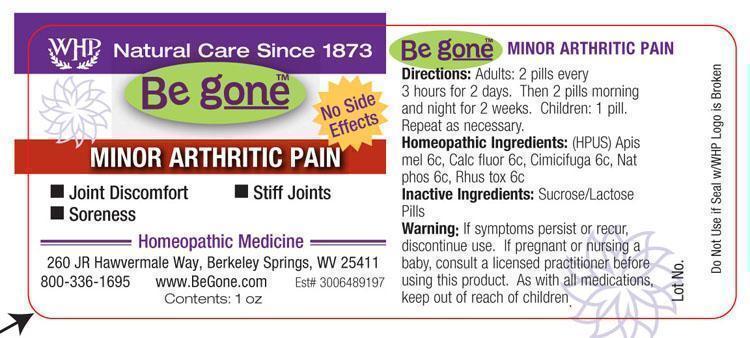 DRUG LABEL: WHP Be gone Minor Arthritic Pain
NDC: 68428-728 | Form: PELLET
Manufacturer: Washington Homeopathic Products
Category: homeopathic | Type: HUMAN OTC DRUG LABEL
Date: 20191223

ACTIVE INGREDIENTS: APIS MELLIFERA 6 [hp_C]/28 g; BLACK COHOSH 6 [hp_C]/28 g; CALCIUM FLUORIDE 6 [hp_C]/28 g; SODIUM PHOSPHATE, DIBASIC, HEPTAHYDRATE 6 [hp_C]/28 g; TOXICODENDRON PUBESCENS LEAF 6 [hp_C]/28 g
INACTIVE INGREDIENTS: SUCROSE; LACTOSE

DRUG FACTS

ACTIVE INGREDIENTS

APIS MEL 6C

CALC FLUOR 6C

CIMICIFUGA 6C

NAT PHOS 6C

RHUS TOX 6C

USES

Temporarily relieves joint discomfort, soreness and stiff joints associated with minor arthritic pain.

KEEP OUT OF REACH OF CHILDREN

As with all medications, keep out of reach of children.

INDICATIONS

APIS MEL Stiffness

CALC FLUOR Enlargement of joints

CIMICIFUGA Aching

NAT PHOS Pain in knees

RHUS TOX Minor arthritic pain

STOP USE AND ASK DOCTOR

If symptoms persist or recur, discontinue use. If pregnant or nursing a baby, consult a licensed practitioner before using this product.

DIRECTIONS

Adults 2 pills every 3 hours for 2 days. Then 2 pills morning and night for 2 weeks.

Children: 1 pill. Repeat as necessary.

INACTIVE INGREDIENTS

Sucrose/Lactose

PRINCIPAL DISPLAY PANEL

WHP Be g oneTM Minor Arthritc Pain Label and Box